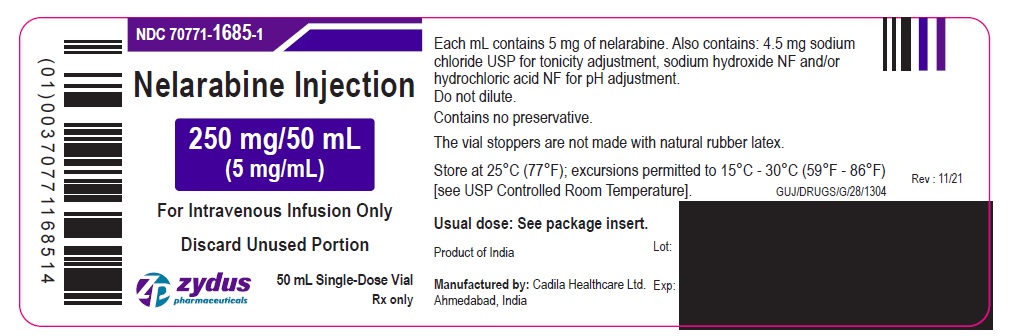 DRUG LABEL: Nelarabine
NDC: 70771-1685 | Form: INJECTION
Manufacturer: Zydus Lifesciences Limited
Category: prescription | Type: HUMAN PRESCRIPTION DRUG LABEL
Date: 20221105

ACTIVE INGREDIENTS: NELARABINE 5 mg/1 mL
INACTIVE INGREDIENTS: HYDROCHLORIC ACID; SODIUM CHLORIDE; SODIUM HYDROXIDE; WATER

NELARABINE INJECTION

.

PACKAGE LABEL.PRINCIPAL DISPLAY PANEL

NDC 70771-1685-1

Nelarabine Injection 250 mg/5 mL (5 mg/mL)

50 mL Single-Dose Vial

For Intravenous Infusion Only

Rx Only

NDC 70771-1685-1

Nelarabine Injection 250 mg/5 mL (5 mg/mL)

50 mL Single-Dose Vial Carton

For Intravenous Infusion Only

Rx Only